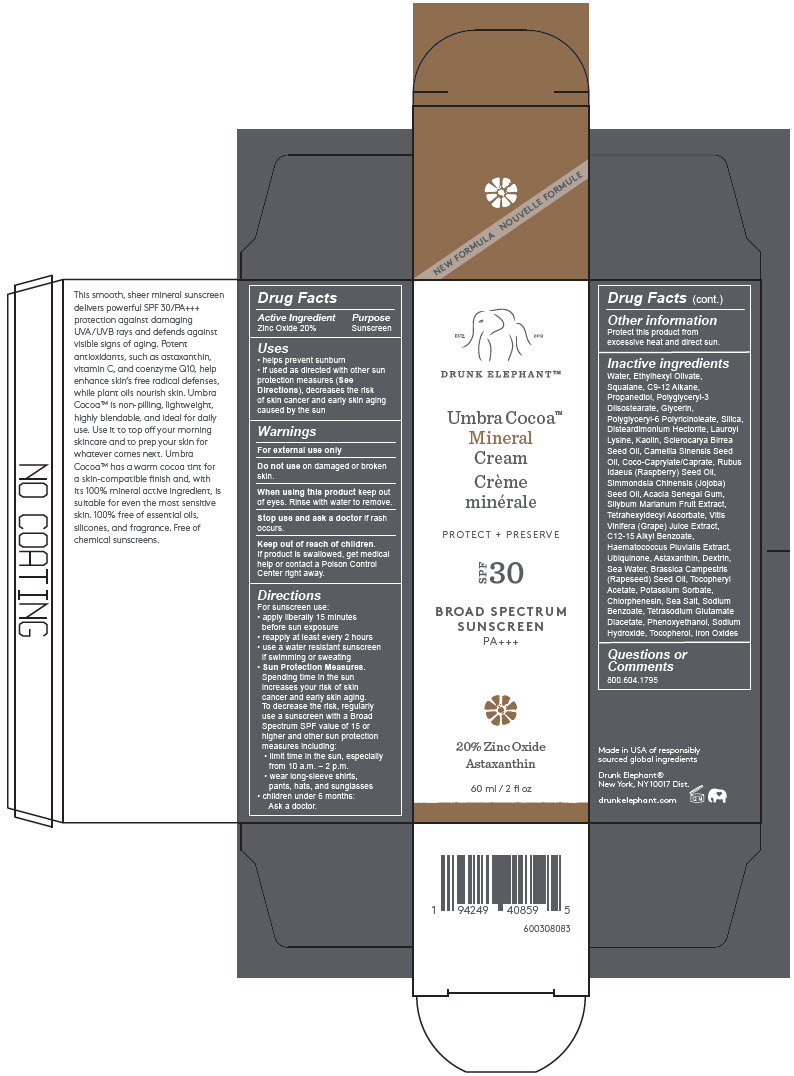 DRUG LABEL: Umbra Cocoa Mineral Cream SPF 30
NDC: 69455-166 | Form: CREAM
Manufacturer: Drunk Elephant, LLC
Category: otc | Type: HUMAN OTC DRUG LABEL
Date: 20260106

ACTIVE INGREDIENTS: ZINC OXIDE 12 g/60 mL
INACTIVE INGREDIENTS: WATER; ETHYLHEXYL OLIVATE; SQUALANE; C9-12 ALKANE; PROPANEDIOL; POLYGLYCERYL-3 DIISOSTEARATE; GLYCERIN; POLYGLYCERYL-6 POLYRICINOLEATE; SILICON DIOXIDE; DISTEARDIMONIUM HECTORITE; LAUROYL LYSINE; KAOLIN; SCLEROCARYA BIRREA SEED OIL; CAMELLIA SINENSIS SEED OIL; COCOYL CAPRYLOCAPRATE; RASPBERRY SEED OIL; JOJOBA OIL; ACACIA; MILK THISTLE; TETRAHEXYLDECYL ASCORBATE; WINE GRAPE JUICE; ALKYL (C12-15) BENZOATE; HAEMATOCOCCUS PLUVIALIS; UBIDECARENONE; ASTAXANTHIN; ICODEXTRIN; SODIUM CHLORIDE; BRASSICA RAPA SUBSP. OLEIFERA OIL; .ALPHA.-TOCOPHEROL ACETATE; POTASSIUM SORBATE; CHLORPHENESIN; SEA SALT; SODIUM BENZOATE; TETRASODIUM GLUTAMATE DIACETATE; PHENOXYETHANOL; SODIUM HYDROXIDE; TOCOPHEROL; FERRIC OXIDE RED

UMBRA COCOA™ MINERAL CREAM SPF 30

Drug Facts

Active Ingredient

Zinc Oxide 20%

Purpose

Sunscreen

Uses

- helps prevent sunburn
- if used as directed with other sun protection measures (See Directions), decreases the risk of skin cancer and early skin aging caused by the sun

Warnings

For external use only

Do not useon damaged or broken skin.

WHEN USING

When using this productkeep out of eyes. Rinse with water to remove.

Stop use and ask a doctorif rash occurs.

Keep out of reach of children.

If product is swallowed, get medical help or contact a Poison Control Center right away.

Directions

For sunscreen use:

- apply liberally 15 minutes before sun exposure
- reapply at least every 2 hours
- use a water resistant sunscreen if swimming or sweating
- Sun Protection Measures.Spending time in the sun increases your risk of skin cancer and early skin aging. To decrease the risk, regularly use a sunscreen with a Broad Spectrum SPF value of 15 or higher and other sun protection measures including:
  - limit time in the sun, especially from 10 a.m. – 2 p.m.
  - wear long-sleeve shirts, pants, hats, and sunglasses
- children under 6 months:
  Ask a doctor.

Other information

Protect this product from excessive heat and direct sun.

Inactive ingredients

Water, Ethylhexyl Olivate, Squalane, C9-12 Alkane, Propanediol, Polyglyceryl-3 Diisostearate, Glycerin, Polyglyceryl-6 Polyricinoleate, Silica, Disteardimonium Hectorite, Lauroyl Lysine, Kaolin, Sclerocarya Birrea Seed Oil, Camellia Sinensis Seed Oil, Coco-Caprylate/Caprate, Rubus Idaeus (Raspberry) Seed Oil, Simmondsia Chinensis (Jojoba) Seed Oil, Acacia Senegal Gum, Silybum Marianum Fruit Extract, Tetrahexyldecyl Ascorbate, Vitis Vinifera (Grape) Juice Extract, C12-15 Alkyl Benzoate, Haematococcus Pluvialis Extract, Ubiquinone, Astaxanthin, Dextrin, Sea Water, Brassica Campestris (Rapeseed) Seed Oil, Tocopheryl Acetate, Potassium Sorbate, Chlorphenesin, Sea Salt, Sodium Benzoate, Tetrasodium Glutamate Diacetate, Phenoxyethanol, Sodium Hydroxide, Tocopherol, Iron Oxides

Questions or Comments

800.604.1795

PRINCIPAL DISPLAY PANEL - 60 ml Tube Box

ESTD
2012

DRUNK ELEPHANT™

Umbra Cocoa™
Mineral
Cream

PROTECT + PRESERVE

SPF
30

BROAD SPECTRUM
SUNSCREEN
PA+++

20% Zinc Oxide
Astaxanthin

60 ml / 2 fl oz